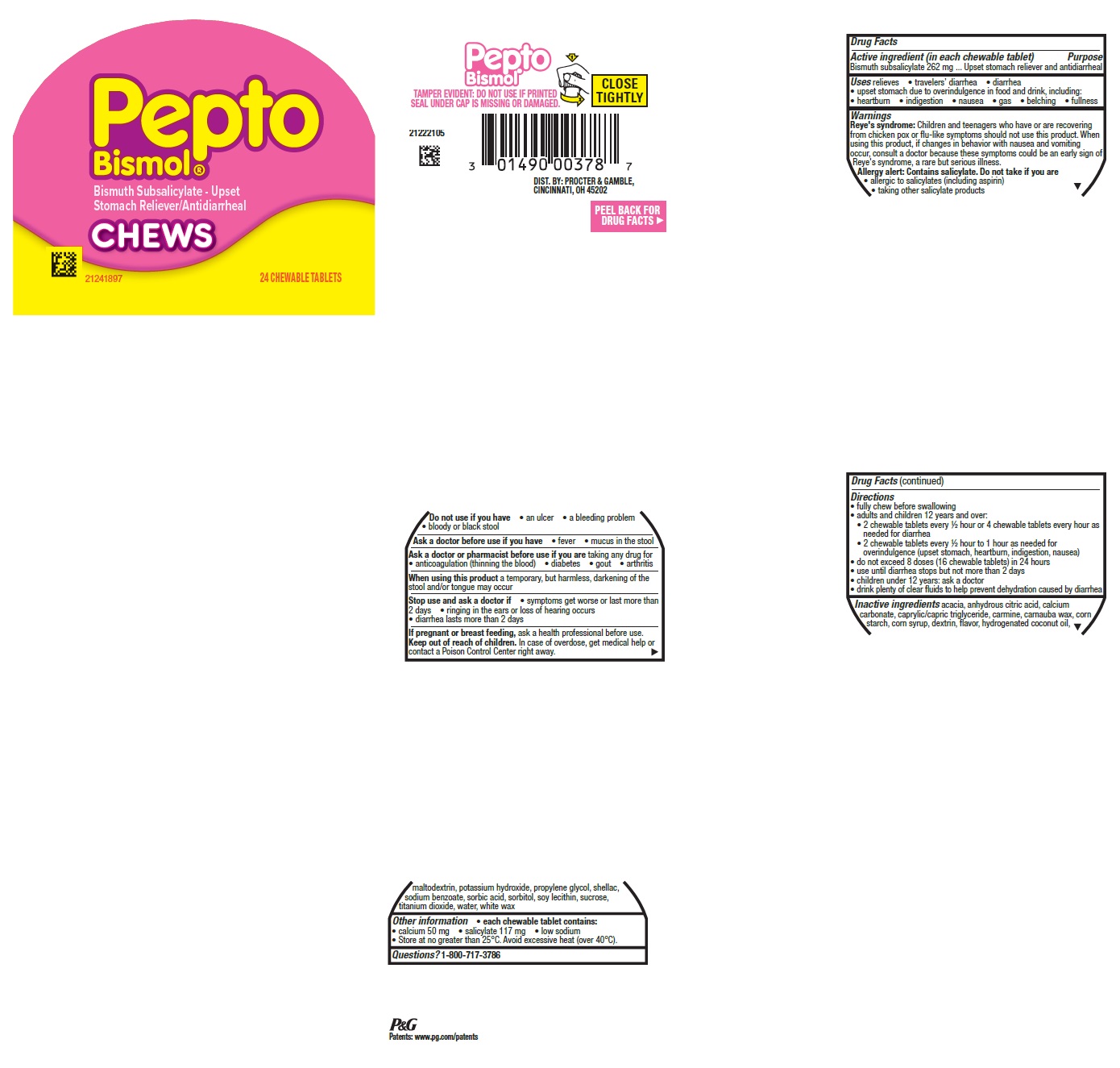 DRUG LABEL: Pepto Bismol
NDC: 37000-996 | Form: TABLET, CHEWABLE
Manufacturer: The Procter & Gamble Manufacturing Company
Category: otc | Type: HUMAN OTC DRUG LABEL
Date: 20251120

ACTIVE INGREDIENTS: BISMUTH SUBSALICYLATE 262 mg/1 1
INACTIVE INGREDIENTS: PROPYLENE GLYCOL; SORBIC ACID; WATER; HYDROGENATED COCONUT OIL; SORBITOL; ICODEXTRIN; ACACIA; WHITE WAX; CALCIUM CARBONATE; CARNAUBA WAX; STARCH, CORN; CORN SYRUP; SODIUM BENZOATE; MALTODEXTRIN; POTASSIUM HYDROXIDE; SHELLAC; CARMINIC ACID; TITANIUM DIOXIDE; SUCROSE; CAPRYLIC/CAPRIC TRIGLYCERIDE; SOYBEAN LECITHIN; ANHYDROUS CITRIC ACID

Pepto Bismol® Chews

Drug Facts

Active ingredient (in each chewable tablet)

Bismuth subsalicylate 262 mg

Purposes

Upset stomach reliever and antidiarrheal

Uses

relieves

- travelers' diarrhea
- diarrhea
- upset stomach due to overindulgence in food and drink, including:
  - heartburn
  - indigestion
  - nausea
  - gas
  - belching
  - fullness

Warnings

Reye's syndrome:

Children and teenagers who have or are recovering from chicken pox or flu-like symptoms should not use this product. When using this product, if changes in behavior with nausea and vomiting occur, consult a doctor because these symptoms could be an early sign of Reye's syndrome, a rare but serious illness.

Allergy alert:

Contains salicylate. Do not take if you are

- allergic to salicylates (including aspirin)
- taking other salicylate products

Do not use if you have

- an ulcer
- a bleeding problem
- bloody or black stool

Ask a doctor before use if you have

- fever
- mucus in the stool

Ask a doctor or pharmacist before use if you are taking any drug for

- anticoagulation (thinning the blood)
- diabetes
- gout
- arthritis

When using this product

a temporary, but harmless, darkening of the stool and/or tongue may occur

Stop use and ask a doctor if

- symptoms get worse or last more than 2 days
- ringing in the ears or loss of hearing occurs
- diarrhea lasts more than 2 days

If pregnant or breast feeding,

ask a health professional before use.

Keep out of reach of children.

OVERDOSAGE

In case of overdose, get medical help or contact a Poison Control Center right away.

Directions

- fully chew before swallowing
- adults and children 12 years and over:
- 2 chewable tablets every ½ hour or 4 chewable tablets every hour as needed for diarrhea
- 2 chewable tablets every ½ hour to 1 hour as needed for overindulgence (upset stomach, heartburn, indigestion, nausea)
- do not exceed 8 doses (16 chewable tablets) in 24 hours
- use until diarrhea stops but not more than 2 days
- children under 12 years: ask a doctor
- drink plenty of clear fluids to help prevent dehydration caused by diarrhea

Other information

• each chewable tablet contains:
• calcium 50 mg • salicylate 117 mg • low sodium
• Store at no greater than 25°C. Avoid excessive heat (over 40°C.)

Inactive ingredients

acacia, anhydrous citric acid, calcium carbonate, caprylic/capric triglyceride, carmine, carnauba wax, corn starch, corn syrup, dextrin, flavor, hydrogenated coconut oil, maltodextrin, potassium hydroxide, propylene glycol, shellac, sodium benzoate, sorbic acid, sorbitol, soy lecithin, sucrose, titanium dioxide, water, white wax

Questions?

1-800-717-3786

TAMPER EVIDENT: DO NOT USE IF PRINTED SEAL UNDER CAP IS MISSING OR DAMAGED.

DIST. BY PROCTER & GAMBLE,
CINCINNATI OH 45202

PRINCIPAL DISPLAY PANEL - 24 CHEWABLE TABLETS

Pepto Bismol®

Bismuth Subsalicylate - Upset Stomach Reliever/Antidiarrheal

CHEWS

24 CHEWABLE TABLETS